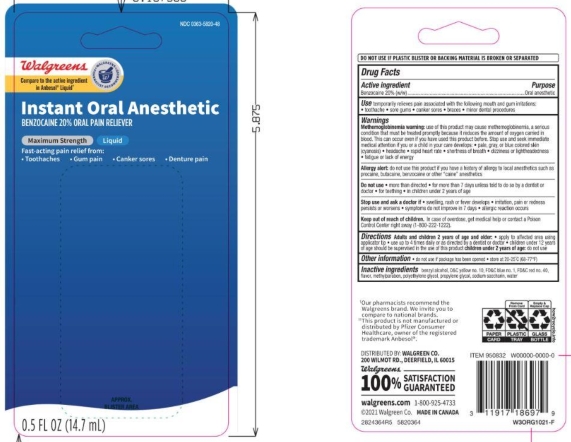 DRUG LABEL: Walgreens
NDC: 0363-5820 | Form: LIQUID
Manufacturer: Walgreens
Category: otc | Type: HUMAN OTC DRUG LABEL
Date: 20250812

ACTIVE INGREDIENTS: BENZOCAINE 20 g/100 g
INACTIVE INGREDIENTS: BENZYL ALCOHOL; FD&C RED NO. 40; D&C YELLOW NO. 10; FD&C BLUE NO. 1; WATER; POLYETHYLENE GLYCOL, UNSPECIFIED; PROPYLENE GLYCOL; SACCHARIN SODIUM; METHYLPARABEN

5820364 Walgreens Instant Oral Pain Relief Liquid

Drug Facts

Active ingredient

Benzocaine 20.0% (w/w)

Purpose

Oral anesthetic

Uses

Temporarily relieves pain associated with the following mouth irritations:

- toothache
- sore gums
- canker sores
- braces
- minor dental procedures

Warnings

Allergy alert: do not use this product if you have a history of allergy to local anesthetics such as procaine, butacaine, benzocaine or other “caine” anesthetics

When using this product

- avoid contact with eyes
- do not exceed recommended dosage
- do not use more than directed for more than 7 days unless directed by a dentist or doctor.

Stop use and ask a doctor or dentist if

- sore mouth symptoms do not improve in 7 days
- irritation, pain or redness persists or worsens
- swelling, rash or fever develops

Keep out of reach of children. If swallowed, get medical help or contact a Poison Control Center right away.

Directions

Adults and children 2 years of age and older:

- apply to affect4ed area using applicator tip
- use up to 4 times daily or as directed by a dentist or doctor.
- children under 12 years of age should be supervised in the use of this product.

children under 2 years of age: ask a dentist or doctor.

Other information

- do not use if package has been opened
- tore at 20-25°C (68-77°F)

INACTIVE INGREDIENT

Inactive ingredients Benzyl Alcohol, D&C Yellow no. 10, FD&C Blue no. 1, FD&C Red no. 40, Methylparaben, Natural and Artificial Flavor, Polyethylene Glycol, Propylene Glycol, Sodium Saccharin, Water

Questions or comments? 1-800-925-4733

DISTRIBUTED BY: WALGREEN CO.

200 WILMOT RD. DEERFIELD, IL 60015

100% SATISFACTION GUARANTEED

www.walgreens.com

MADE IN CANADA